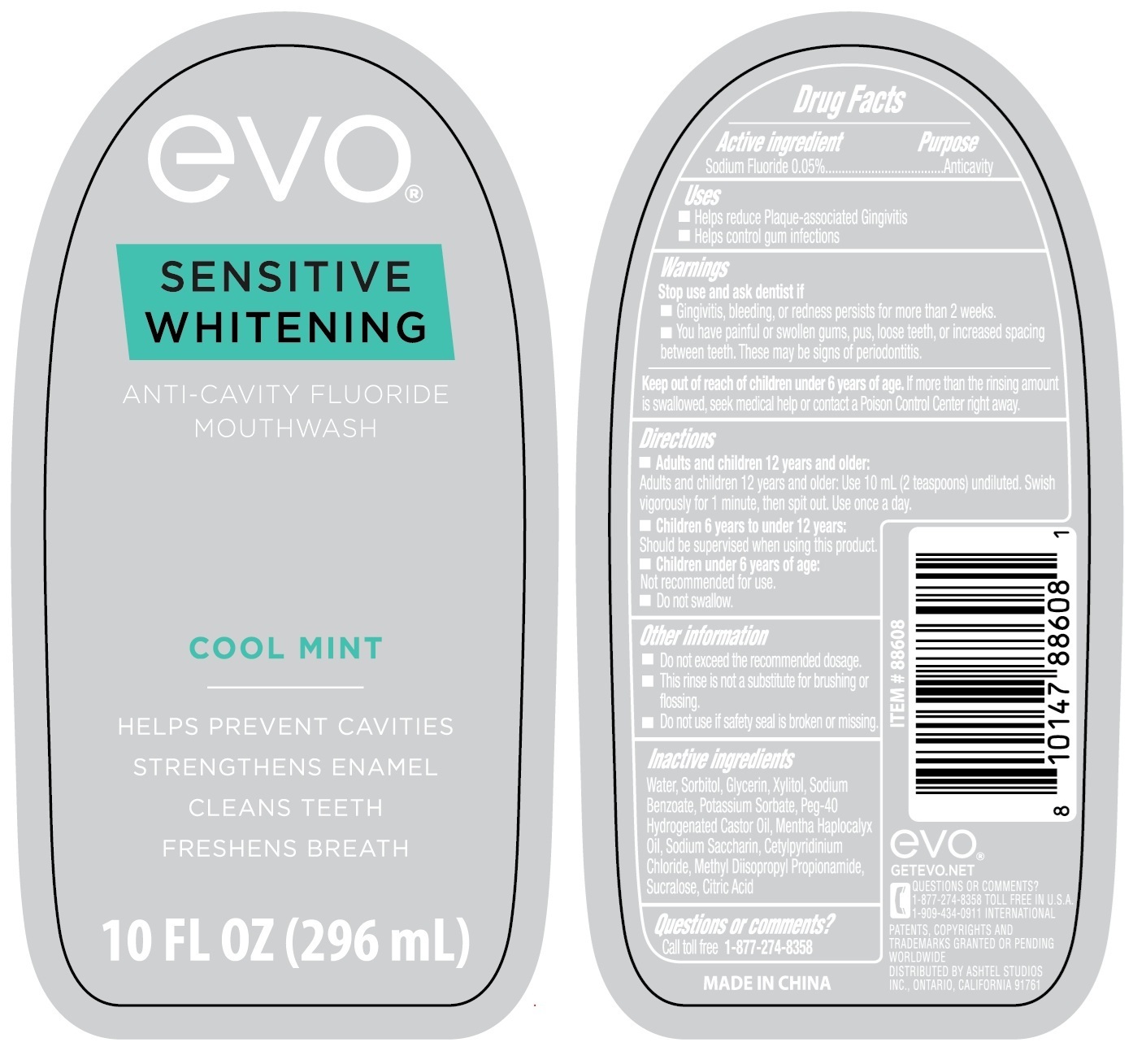 DRUG LABEL: evo SENSITIVE WHITENING ANTI-CAVITY FLUORIDE
NDC: 70108-210 | Form: MOUTHWASH
Manufacturer: Ashtel Studios, Inc.
Category: otc | Type: HUMAN OTC DRUG LABEL
Date: 20250715

ACTIVE INGREDIENTS: SODIUM FLUORIDE 0.05 g/100 mL
INACTIVE INGREDIENTS: WATER; SORBITOL; GLYCERIN; XYLITOL; SODIUM BENZOATE; POTASSIUM SORBATE; POLYOXYL 40 HYDROGENATED CASTOR OIL; MENTHA CANADENSIS TOP OIL; SACCHARIN SODIUM; CETYLPYRIDINIUM CHLORIDE; METHYL DIISOPROPYL PROPIONAMIDE; SUCRALOSE; CITRIC ACID MONOHYDRATE

evo® SENSITIVE WHITENING ANTI-CAVITY FLUORIDE MOUTHWASH

Active ingredient

Sodium Fluoride 0.05%

Purpose

Anticavity

Uses

• Helps reduce Plaque-associated Gingivitis
• Helps control gum infections

Warnings

Stop use and ask dentist if
• Gingivitis, bleeding, or redness persists for more than 2 weeks.
• You have painful or swollen gums, pus, loose teeth, or increased spacing between teeth. These may be signs of periodontitis.

Keep out of reach of children under 6 years of age. If more than the rinsing amount is swallowed, seek medical help or contact a Poison Control Center right away.

Directions

• Adults and children 12 years and older:
Adults and children 12 years and older: Use 10 mL (2 teaspoons) undiluted. Swish vigorously for 1 minute, then spit out. Use once a day.

• Children 6 years to under 12 years:
Should be supervised when using this product.

• Children under 6 years of age:
Not recommended for use.

• Do not swallow.

Other information

• Do not exceed the recommended dosage.
• This rinse is not a substitute for brushing or flossing.
• Do not use if safety seal is broken or missing.

Inactive ingredients

Water, Sorbitol, Glycerin, Xylitol, Sodium Benzoate, Potassium Sorbate, Peg-40 Hydrogenated Castor Oil, Mentha Haplocalyx Oil, Sodium Saccharin, Cetylpyridinium Chloride, Methyl Diisopropyl Propionamide, Sucralose, Citric Acid

Questions or comments?

Call toll free 1-877-274-8358

COOL MINT

HELPS PREVENT CAVITIES

STRENGTHS ENAMEL

CLEANS TEETH

FRESHENS BREATH

MADE IN CHINA

GETEVO.NET

1-909-434-0911 INTERNATIONAL

PATENTS, COPYRIGHTS AND TRADEMARKS GRANTED OR PENDING WORLDWIDE

DISTRIBUTED BY ASHTEL STUDIOS INC., ONTARIO, CALIFORNIA 91761